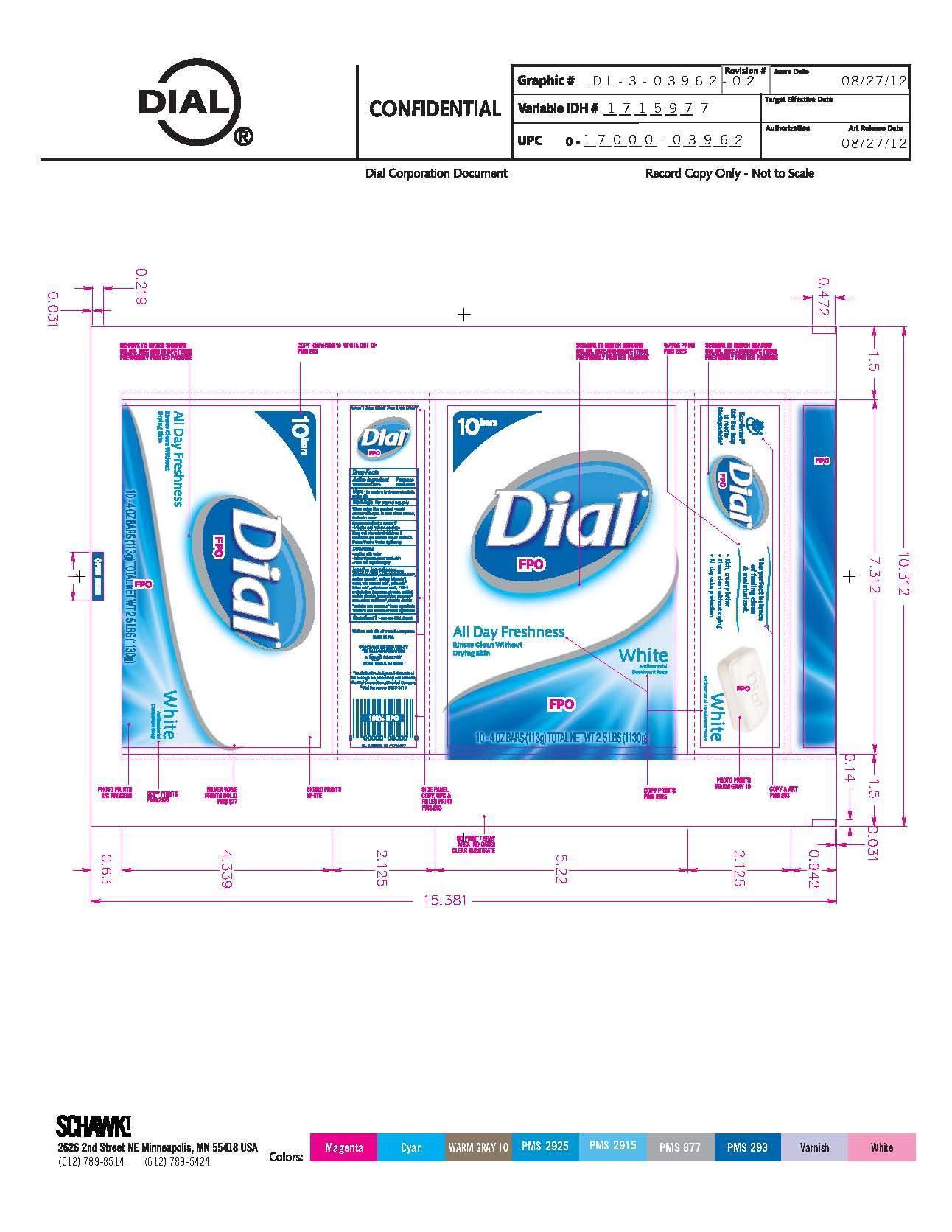 DRUG LABEL: Dial
NDC: 51815-301 | Form: SOAP
Manufacturer: VVF Illinois Services LLC
Category: otc | Type: HUMAN OTC DRUG LABEL
Date: 20140224

ACTIVE INGREDIENTS: TRICLOCARBAN 113 g/113 g
INACTIVE INGREDIENTS: SODIUM COCOATE; SODIUM PALM KERNELATE; SODIUM PALMATE; SODIUM TALLOWATE, BEEF; WATER; TALC; COCONUT ACID; PALM ACID; TALLOW ACID, BEEF; PALM KERNEL ACID; PEG-6 METHYL ETHER; GLYCERIN; SORBITOL; SODIUM CHLORIDE; PENTASODIUM PENTETATE; ETIDRONATE TETRASODIUM; TITANIUM DIOXIDE

Dial White

Active ingredient

Triclocarban 0.30%

Purpose

Antibacterial

Keep out of reach of children.

If swallowed, get medical

help or contact Poison Control right away.

Use

For washing to decrease bacteria on the skin

Warnings

For external use only

When using this product

Avoid contact with eyes. In case of eye contact, flush with water

Stop using and ask doctor if irritation and redness develops

Directions

wet bar with water - lather vigorously -

and wash skin - rinse and dry thoroughly

Inactive ingredients

soap (sodium cocoate*, sodium

palm kernelate*, sodium palmate*, sodium tallowate*), water, talc

coconut acid*, palm acid*, tallow acid*, palm kernel acid*, PEG-6 methyl

ether, fragrance, glycerin, sorbitol, sodium chloride, pentasodium

pentate1, tetra sodium etidronate1, yellow 5, yellow 8, red 4

*contains one or more of these ingredients

1contains one or more of these ingredients